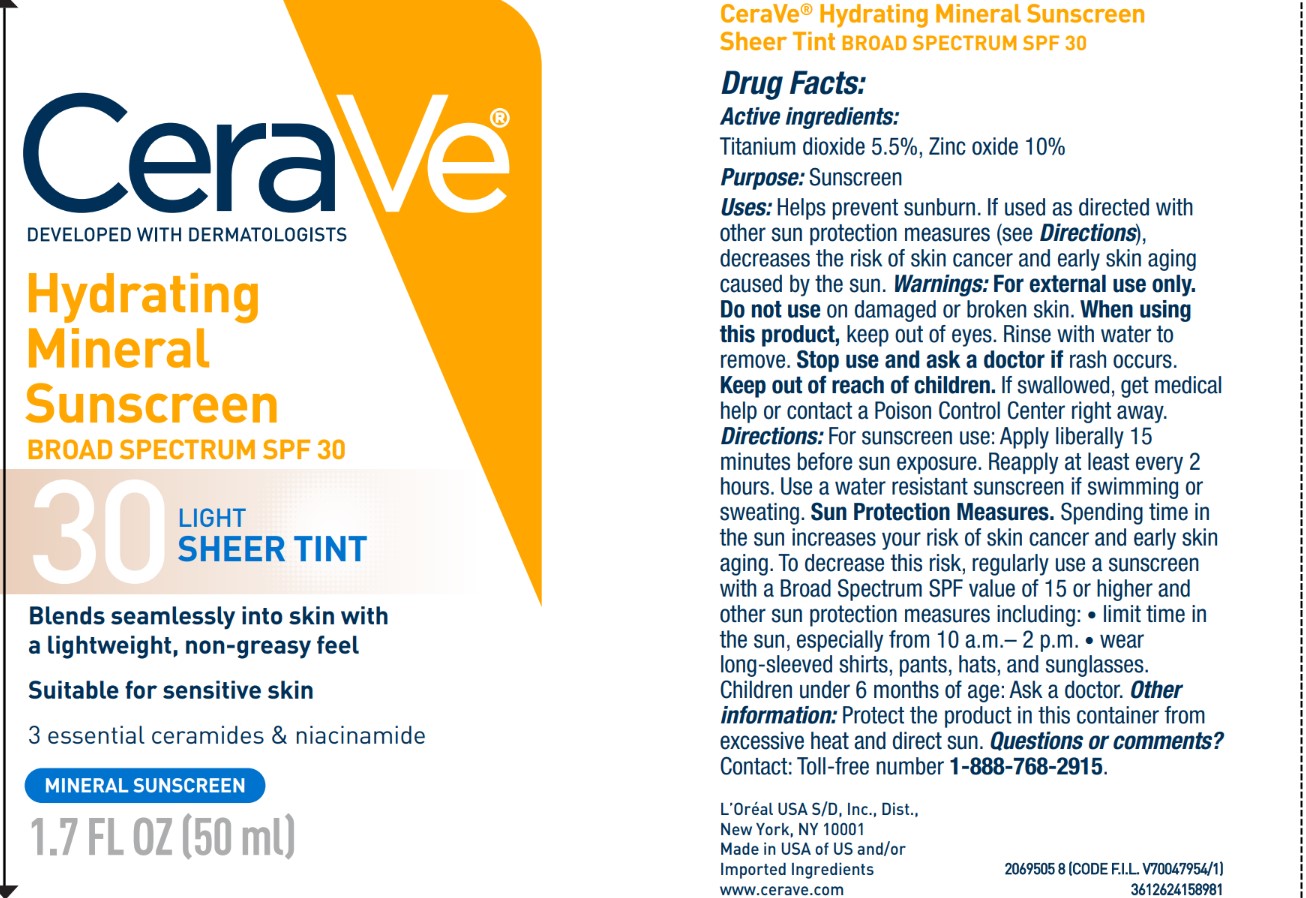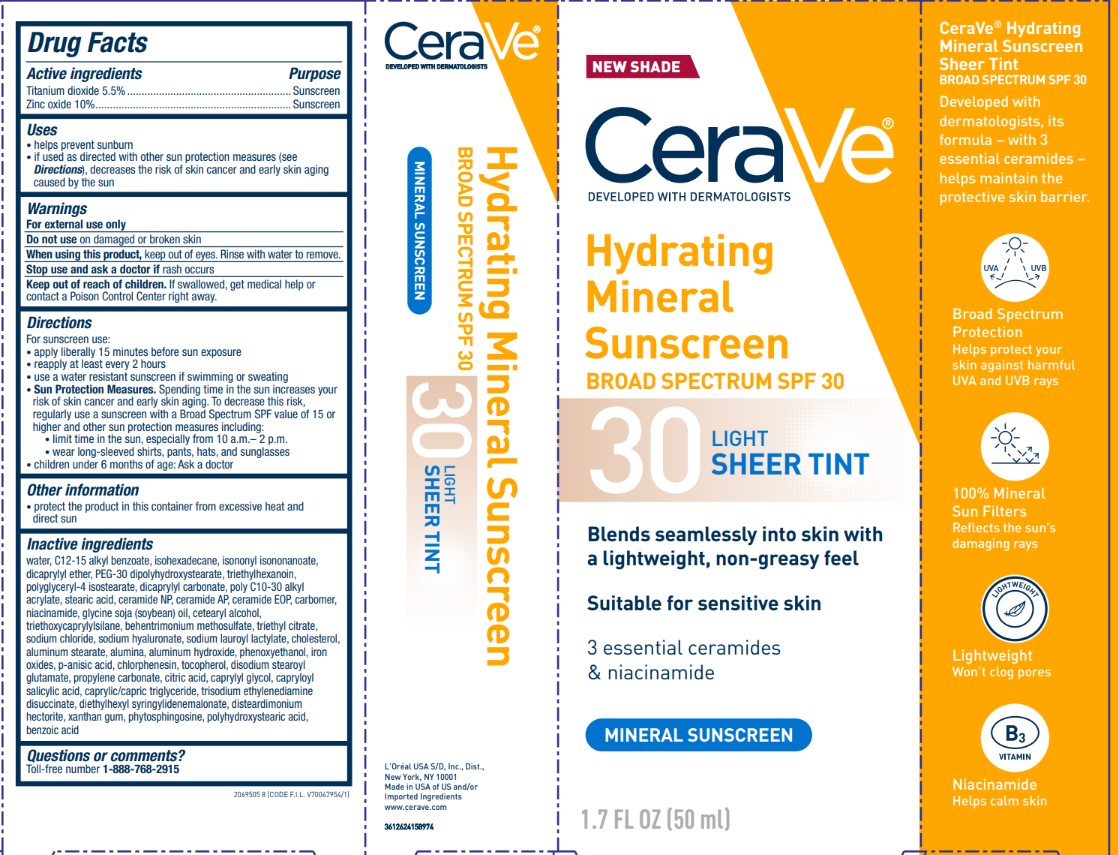 DRUG LABEL: CERAVE Hydrating Mineral Sunscreen Light Sheer Tint Broad Spectrum SPF 30
NDC: 49967-589 | Form: LOTION
Manufacturer: L’Oreal USA Products Inc
Category: otc | Type: HUMAN OTC DRUG LABEL
Date: 20241223

ACTIVE INGREDIENTS: TITANIUM DIOXIDE 55 mg/1 mL; ZINC OXIDE 100 mg/1 mL
INACTIVE INGREDIENTS: WATER; C12-15 ALKYL BENZOATE; ISOHEXADECANE; ISONONYL ISONONANOATE; DICAPRYLYL ETHER; PEG-30 DIPOLYHYDROXYSTEARATE; TRIETHYLHEXANOIN; POLYGLYCERYL-4 ISOSTEARATE; DICAPRYLYL CARBONATE; BEHENYL ACRYLATE POLYMER; STEARIC ACID; CERAMIDE NP; CERAMIDE AP; CARBOMER; NIACINAMIDE; SOYBEAN OIL; CETEARYL ALCOHOL; TRIETHOXYCAPRYLYLSILANE; BEHENTRIMONIUM METHOSULFATE; TRIETHYL CITRATE; SODIUM CHLORIDE; SODIUM HYALURONATE; SODIUM LAUROYL LACTYLATE; CHOLESTEROL; ALUMINUM STEARATE; ALUMINA; ALUMINUM HYDROXIDE; PHENOXYETHANOL; P-ANISIC ACID; CHLORPHENESIN; TOCOPHEROL; DISODIUM STEAROYL GLUTAMATE; PROPYLENE CARBONATE; CITRIC ACID; CAPRYLYL GLYCOL; CAPRYLOYL SALICYLIC ACID; CAPRYLIC/CAPRIC TRIGLYCERIDE; TRISODIUM ETHYLENEDIAMINE DISUCCINATE; DIETHYLHEXYL SYRINGYLIDENEMALONATE; DISTEARDIMONIUM HECTORITE; XANTHAN GUM; PHYTOSPHINGOSINE; POLYHYDROXYSTEARIC ACID (2300 MW); BENZOIC ACID; CI 77492; CI 77491; CI 77499

Drug Facts

Active ingredients

Titanium dioxide 5.5%

Zinc oxide 10%

Purpose

Sunscreen

Uses

- helps prevent sunburn
- if used as directed with other sun protection measures (see Directions), decreases the risk of skin cancer and early skin aging caused by the sun

Warnings

For external use only

Do not use

on damaged or boken skin

When using this product

keep out of eyes. Rinse with water to remove.

Stop use and ask a doctor if

rash occurs

Keep out of reach of children.

If swallowed, get medical help or contact a Poison Control Center right away.

Directions

For sunscreen use:

- apply liberally 15 minutes before sun exposure
- reapply at least every 2 hours
- use a water resistant sunscreen if swimming or sweating
- Sun Protection Measures. Spending time in the sun increases your risk of skin cancer and early skin aging. To decrease this risk, regularly use a sunscreen with a Broad Spectrum SPF value of 15 or higher and other sun protection measures including:
- limit time in the sun, especially from 10 a.m.- 2 p.m.
- wear long-sleeved shirts, pants, hats, and sunglasses
- children under 6 months of age: Ask a doctor

Other information

- protect the product in this container from excessive heat and direct sun

Inactive ingredients

water, C12-15 alkyl benzoate, isohexadecane, isononyl isononanoate, dicaprylyl ether, PEG-30 dipolyhydroxystearate, polyglyceryl-3 diisostearate, ceramide NP, ceramide AP, ceramide EOP, carbomer, acrylates/C10-30 alkyl acrylate crosspolymer, triethanolamine, alkyl sodium chloride, glycine soja (soybean) oil, cetearyl alcohol, triethylhexanoin, behentrimonium methosulfate, lauryl laurate, cholesterol, aluminum stearate, chlorphenesin, tocopherol, disodium EDTA, iron oxides, p-anisic acid, alumina, aluminum hydroxide, phenoxyethanol, salicylic acid, capryloyl salicylic acid, trisodium ethylenediamine disuccinate, propylene carbonate, citric acid, castoryl dimethyl caprate, distearyldimonium chloride, glyceryl trilinoleate, disteardimonium hectorite, xanthan gum, phytosphingosine, polyhydroxystearic acid, benzoic acid

Questions or comments?

Toll-free number: 1-888-768-2915